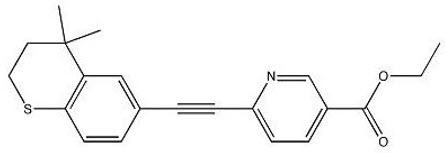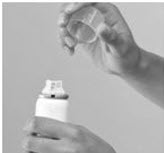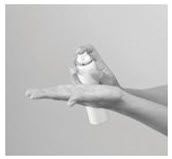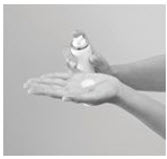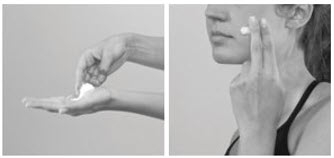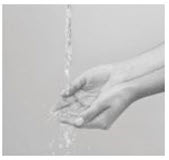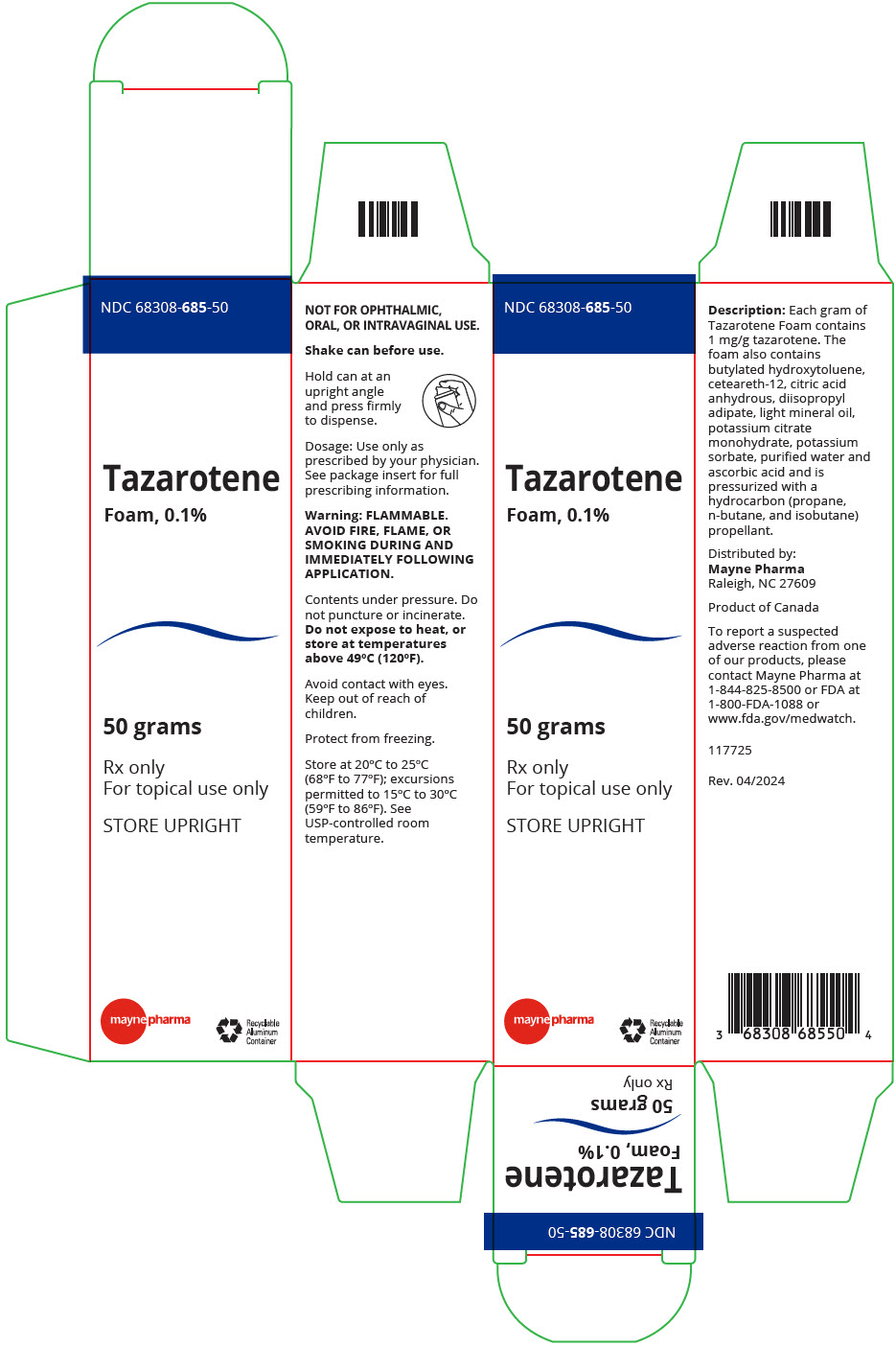 DRUG LABEL: tazarotene
NDC: 68308-685 | Form: AEROSOL, FOAM
Manufacturer: Mayne Pharma Inc.
Category: prescription | Type: HUMAN PRESCRIPTION DRUG LABEL
Date: 20240604

ACTIVE INGREDIENTS: tazarotene 1 mg/1 g
INACTIVE INGREDIENTS: BUTYLATED HYDROXYTOLUENE; CETEARETH-12; ANHYDROUS CITRIC ACID; DIISOPROPYL ADIPATE; LIGHT MINERAL OIL; POTASSIUM CITRATE; POTASSIUM SORBATE; WATER; SORBIC ACID

HIGHLIGHTS OF PRESCRIBING INFORMATION

These highlights do not include all the information needed to use Tazarotene Foam safely and effectively. See full prescribing information for Tazarotene Foam.
Tazarotene Foam, 0 .1%, for topical use
Initial U.S. Approval: 1997

1 INDICATIONS AND USAGE

Tazarotene Foam is a retinoid indicated for the topical treatment of acne vulgaris in patients 12 years of age or older. (1)

2 DOSAGE AND ADMINISTRATION

- Apply a thin layer to the entire affected areas of the face and/or upper trunk once daily in the evening. Avoid the eyes, lips, and mucous membranes. Wash hands after application. (2)

3 DOSAGE FORMS AND STRENGTHS

- 0.1%, foam. (3)

4 CONTRAINDICATIONS

- Pregnancy. (4, 8.1)

5 WARNINGS AND PRECAUTIONS

- Fetal Risk: Tazarotene Foam contains tazarotene, which is a teratogenic substance. Tazarotene Foam is contraindicated in pregnancy. Females of childbearing potential should have a negative pregnancy test within 2 weeks prior to initiating treatment and use an effective method of contraception during treatment. (5.1)
- Local Irritation: Use with caution in patients with a history of local tolerability reactions or local hypersensitivity. (5.2)
- Potential Irritant Effect with Concomitant Topical Medications: Use with caution because a cumulative irritant effect may occur. (5.3)
- Photosensitivity and Risk for Sunburn: Avoid exposure to sunlight, sunlamps, and weather extremes. Wear sunscreen daily. (5.4)
- Contents are flammable. Instruct the patient to avoid fire, flame, and smoking during and immediately following application. (5.5)

6 ADVERSE REACTIONS

- Most common adverse reactions reported at an incidence ≥6% are application site irritation, application site dryness, application site erythema, and application site exfoliation. (6.1)

To report SUSPECTED ADVERSE REACTIONS, contact Mayne Pharma at 1-844-825-8500 or FDA at 1-800-FDA-1088 or www.fda.gov/medwatch

7 DRUG INTERACTIONS

- Avoid concomitant dermatologic medications and cosmetics that have a strong drying effect. (7)

FULL PRESCRIBING INFORMATION

1 INDICATIONS AND USAGE

Tazarotene Foam, 0.1% is indicated for the topical treatment of acne vulgaris in patients 12 years of age or older.

2 DOSAGE AND ADMINISTRATION

Tazarotene Foam is for topical use only. Tazarotene Foam is not for oral, ophthalmic, or intravaginal use.

Tazarotene Foam should be applied once daily in the evening after washing with a mild cleanser and fully drying the affected area. Dispense a small amount of foam into the palm of the hand. Using fingertips, apply only enough foam to lightly cover the entire affected areas of the face and/or upper trunk with a thin layer; gently massage the foam into the skin until the foam disappears. Avoid the eyes, lips, and mucous membranes. Wash hands after application.

Patients may use moisturizer as needed.

If undue irritation (redness, peeling, or discomfort) occurs, patients should reduce frequency of application or temporarily interrupt treatment. Treatment may be resumed once irritation subsides. Treatment should be discontinued if irritation persists.

3 DOSAGE FORMS AND STRENGTHS

0.1%, white to off-white foam

4 CONTRAINDICATIONS

Tazarotene Foam is contraindicated in pregnancy.

Tazarotene Foam may cause fetal harm when administered to a pregnant woman. Tazarotene elicits teratogenic and developmental effects associated with retinoids after topical or systemic administration in rats and rabbits [see Use in Specific Populations (8.1, 8.3)].

If this drug is used during pregnancy, or if the patient becomes pregnant while taking this drug, treatment should be discontinued and the patient apprised of the potential hazard to the fetus [see Warnings and Precautions (5.1), Use in Specific Populations (8.1, 8.3)].

5 WARNINGS AND PRECAUTIONS

5.1 Fetal Risk

Systemic exposure to tazarotenic acid is dependent upon the extent of the body surface area treated. In patients treated topically over sufficient body surface area, exposure could be in the same order of magnitude as in orally treated animals. Tazarotene is a teratogenic substance, and it is not known what level of exposure is required for teratogenicity in humans [see Clinical Pharmacology (12)].

There were 5 reported pregnancies in subjects who participated in clinical trials for topical tazarotene foam. One of the subjects was found to have been treated with topical tazarotene for 25 days, 2 were treated with vehicle foam, and the other 2 did not receive either tazarotene foam or vehicle foam. The subjects were discontinued from the trials when their pregnancy was reported. The one pregnant woman who was inadvertently exposed to topical tazarotene during the clinical trial delivered a full-term healthy infant.

Females of Childbearing Potential:

Females of child-bearing potential should be warned of the potential risk and use adequate birth-control measures when tazarotene foam is used. The possibility of pregnancy should be considered in females of child-bearing potential at the time of institution of therapy.

A negative serum or urine result for pregnancy test having a sensitivity down to at least 25 mIU/mL for human chorionic gonadotropin (hCG) should be obtained within 2 weeks prior to therapy with Tazarotene Foam, which should begin during a normal menstrual period for females of childbearing potential. Advise patients of the need to use an effective method of contraception to avoid pregnancy [see Use in Specific Populations (8.1, 8.3)].

5.2 Local Irritation

Tazarotene Foam should be used with caution in patients with a history of local tolerability reactions or local hypersensitivity. Retinoids should not be used on abraded or eczematous skin, as they may cause severe irritation. Contact with the mouth, eyes, and mucous membranes should be avoided. In case of accidental contact, rinse well with water.

Some individuals may experience skin redness, peeling, burning or excessive pruritus. If these effects occur, the medication should either be discontinued until the integrity of the skin is restored, or the dosing should be reduced to an interval the patient can tolerate. However, efficacy at reduced frequency of application has not been established.

Weather extremes, such as wind or cold, may be more irritating to patients using Tazarotene Foam.

5.3 Potential Irritant Effect with Concomitant Topical Medications

Concomitant topical acne therapy should be used with caution because a cumulative irritant effect may occur. If irritancy or dermatitis occurs, reduce frequency of application or temporarily interrupt treatment and resume once the irritation subsides. Treatment should be discontinued if the irritation persists.

5.4 Photosensitivity and Risk for Sunburn

Because of heightened burning susceptibility, exposure to sunlight (including sunlamps) should be avoided. Patients must be warned to use sunscreens and protective clothing when using Tazarotene Foam. Patients with sunburn should be advised not to use Tazarotene Foam until fully recovered. Patients who may have considerable sun exposure due to their occupation and those patients with inherent sensitivity to sunlight should exercise particular caution when using Tazarotene Foam and ensure that the precautions are observed [see FDA-approved patient labeling]. Due to the potential for photosensitivity resulting in greater risk for sunburn, Tazarotene Foam should be used with caution in patients with a personal or family history of skin cancer.

Tazarotene Foam should be administered with caution if the patient is also taking drugs known to be photosensitizers (e.g., thiazides, tetracyclines, fluoroquinolones, phenothiazines, sulfonamides) because of the increased possibility of augmented photosensitivity.

5.5 Flammability

The propellant in Tazarotene Foam is flammable. Instruct the patient to avoid fire, flame, and/or smoking during and immediately following application.

6 ADVERSE REACTIONS

6.1 Clinical Trials Experience

Because clinical trials are conducted under widely varying conditions, adverse reaction rates observed in the clinical trials of a drug cannot be directly compared with rates in the clinical trials of another drug and may not reflect the rates observed in practice.

The safety data reflect exposure to Tazarotene Foam in 744 subjects with acne vulgaris. Subjects were aged 12 to 45 years and were treated once daily in the evening for 12 weeks. Adverse reactions reported in ≥ 1% of subjects treated with Tazarotene Foam are presented in Table 1. Most adverse reactions were mild to moderate in severity. Severe adverse reactions represented 3.0% of the subjects treated. Overall, 2.7% (20/744) of subjects discontinued Tazarotene Foam because of local skin reactions.

Table 1. Incidence of Adverse Reactions in ≥1 % of Subjects Treated with Tazarotene Foam
 | Tazarotene Foam N = 744 | Vehicle Foam N = 741
Patients with any adverse reaction, n (%) | 163 (22) | 19 (3)
Application site irritation | 107 (14) | 9 (1)
Application site dryness | 50 (7) | 8 (1)
Application site erythema | 48 (6) | 3 (<1)
Application site exfoliation | 44 (6) | 3 (<1)
Application site pain | 9 (1) | 0
Application site photosensitivity (including sunburn) | 8 (1) | 3 (<1)
Application site pruritus | 7 (1) | 3 (<1)
Application site dermatitis | 6 (1) | 1 (<1)

Additional adverse reactions that were reported in <1% of subjects treated with Tazarotene Foam included application site reactions (including discoloration, discomfort, edema, rash, and swelling), dermatitis, impetigo, and pruritus.

Local skin reactions, dryness, erythema, and peeling actively assessed by the investigator and burning/stinging and itching reported by the subject were evaluated at baseline, during treatment, and end of treatment. During the 12 weeks of treatment, each local skin reaction peaked at Week 2 and gradually reduced thereafter with the continued use of Tazarotene Foam.

7 DRUG INTERACTIONS

No formal drug-drug interaction studies were conducted with Tazarotene Foam.

Concomitant dermatologic medications and cosmetics that have a strong drying effect should be avoided. It is recommended to postpone treatment until the effects of these products subside before use of Tazarotene Foam is started.

Concomitant use with oxidizing agents, such as benzoyl peroxide, may cause degradation of tazarotene and may reduce the clinical efficacy of tazarotene. If combination therapy is required, they should be applied at different times of the day (e.g., one in the morning and the other in the evening).

The impact of tazarotene on the pharmacokinetics of progestin-only oral contraceptives (i.e., minipills) has not been evaluated.

In a trial of 27 healthy female subjects between the ages of 20 to 55 years receiving a combination oral contraceptive tablet containing 1 mg norethindrone and 35 mcg ethinyl estradiol, concomitant use of tazarotene did not affect the pharmacokinetics of norethindrone and ethinyl estradiol over a complete cycle.

8 USE IN SPECIFIC POPULATIONS

8.1 Pregnancy

Tazarotene Foam is contraindicated in pregnancy [see Contraindications (4)].

There are no adequate and well -controlled studies with Tazarotene Foam in pregnant women. Tazarotene Foam is contraindicated in females who are or may become pregnant [see Contraindications (4)]. Females of child-bearing potential should be warned of the potential risk and use of adequate birth-control measures when Tazarotene Foam is used. The possibility that a female of child-bearing potential is pregnant at the time of institution of therapy should be considered. A negative serum or urine result for pregnancy test having a sensitivity down to at least 25 mlU/mL for hCG should be obtained within 2 weeks prior to therapy with Tazarotene Foam, which should begin during a normal menstrual period for females of childbearing potential.

In rats, tazarotene 0.05% gel administered topically during gestation days 6 through 17 at 0.25 mg/kg/day resulted in reduced fetal body weights and reduced skeletal ossification. Rabbits dosed topically with 0.25 mg/kg/day tazarotene gel during gestation days 6 through 18 were noted with single incidences of known retinoid malformations, including spina bifida, hydrocephaly, and heart anomalies.

Systemic exposure (AUC) to tazarotenic acid at topical doses of 0.25 mg/kg/day tazarotene in a gel formulation in rats and rabbits were 15 to 166 times, respectively, the AUC in acne patients treated with 2 mg/cm^2 of Tazarotene Foam 0.1% over a 15% body surface acrea.

A with other retinoids, when tazarotene was administered orally to experimental animals, developmental delays were seen in rats, and teratogenic effects and post-implantation loss were observed in rats and rabbits at doses 13 and 325 times, respectively, the AUC to tazarotenic acid in acne patients treated with 2 mg/cm^2 of Tazarotene Foam 0.1% over a 15% body surface area.

In female rats orally administered 2 mg/kg/day tazarotene from 15 days before mating through gestation day 7, a number of classic developmental effects of retinoids were observed including decreased number of implantation sites, decreased litter size, decreased numbers of live fetuses, and decreased fetal body weights. A low incidence of retinoid-related malformations was also observed. AUC in rats was 42 times the AUC in acne patients treated with 2 mg/cm^2 of Tazarotene Foam 0.1% over a 15% body surface area.

8.3 Nursing Mothers

After single topical doses of ^14C-tazarotene to the skin of lactating rats, radioactivity was detected in milk, suggesting that there would be transfer of drug-related material to the offspring via milk. It is not known whether this drug is excreted in human milk. The safe use of Tazarotene Foam during lactation has not been established. A decision should be made whether to discontinue breastfeeding or to discontinue therapy with Tazarotene Foam taking into account the benefit of breastfeeding for the child and the benefit of therapy for the woman.

8.4 Pediatric Use

The safety and effectiveness of Tazarotene Foam in pediatric patients younger than 12 years have not been established. Clinical studies of Tazarotene Foam included 860 patients aged 12 to 17 years with acne vulgaris.

8.5 Geriatric Use

Tazarotene Foam for the treatment of acne has not been clinically evaluated in persons over the age of 65.

10 OVERDOSAGE

Excessive topical application of Tazarotene Foam may lead to marked redness, peeling, or discomfort. [see Warnings and Precautions (5.2)]. Management of accidental ingestion or excessive application to the skin should be as clinically indicated.

11 DESCRIPTION

Tazarotene (tazarotene) Foam, 0.1% contains the compound tazarotene, a member of the acetylenic class of retinoids. It is for topical use only.

Chemically, tazarotene is ethyl 6-[(4,4-dimethylthiochroman-6-yl)ethynyl]nicotinate. The structural formula is represented below:

Molecular Formula: C21H21NO2S Molecular Weight: 351.46

Tazarotene is a pale yellow to yellow substance. Tazarotene Foam contains tazarotene, 1 mg/g, in aqueous-based white to off-white foam vehicle consisting of butylated hydroxytoluene, ceteareth-12, citric acid anhydrous, diisopropyl adipate, light mineral oil, potassium citrate monohydrate, potassium sorbate, purified water, and sorbic acid. Tazarotene Foam is dispensed from an aluminum can pressurized with a hydrocarbon (propane/n-butane/isobutane) propellant.

12 CLINICAL PHARMACOLOGY

12.1 Mechanism of Action

Tazarotene is a retinoid prodrug that is converted to its active form, the cognate carboxylic acid of tazarotene, by rapid deesterification in animals and man. Tazarotenic acid binds to all 3 members of the retinoic acid receptor (RAR) family: RARα, RARβ, and RARγ but shows relative selectivity for RARβ and RARγ and may modify gene expression. The clinical significance of these findings is unknown.

The mechanism of tazarotene action in acne vulgaris is not defined. However, the basis of tazarotene's therapeutic effect in acne may be due to its anti-hyperproliferative, normalizing-of-differentiation and anti-inflammatory effects. Tazarotene inhibited corneocyte accumulation in rhino mouse skin and cross- linked envelope formation in cultured human keratinocytes. The clinical significance of these findings is unknown.

12.2 Pharmacodynamics

The pharmacodynamics of Tazarotene Foam are unknown.

12.3 Pharmacokinetics

Following topical application, tazarotene undergoes esterase hydrolysis to form its active metabolite, tazarotenic acid. Tazarotenic acid was highly bound to plasma proteins (greater than 99%). Tazarotene and tazarotenic acid were metabolized to sulfoxides, sulfones, and other polar metabolites which were eliminated through urinary and fecal pathways.

Systemic exposure following topical application of Tazarotene Foam 0.1% was evaluated in one trial. Patients aged 15 years and older with moderate-to-severe acne applied approximately 3.7 grams of Tazarotene Foam 0.1% (N = 13) to approximately 15% body surface area (face, upper chest, upper back, and shoulders) once daily for 22 days. On Day 22, the mean (±SD) tazarotenic acid Cmax was 0.43 (±0.19) ng/mL, the AUC0-24h was 6.98 (±3.56) ng∙h/mL, and the half-life was 21.7 (±15.7) hours. The median Tmax was 6 hours (range: 4.4 to 12 hours). The AUC0-24h for tazarotenic acid was approximately 50-fold higher compared with the parent compound tazarotene. The mean (±SD) half-life of tazarotene was 8.1 (±3.7) hours.

Accumulation was observed upon repeated once-daily dosing as the tazarotenic acid predose concentrations were measurable in the majority of subjects. Steady state was attained within 22 days of daily application. Once-daily dosing resulted in little to no accumulation of tazarotene as predose concentrations were mostly below the quantitation limit throughout the study.

13 NONCLINICAL TOXICOLOGY

13.1 Carcinogenesis, Mutagenesis, Impairment of Fertility

Carcinogenesis:

A long-term study of tazarotene following oral administration of 0.025, 0.050, and 0.125 mg/kg/day to rats showed no indications of increased carcinogenic risk. Based on pharmacokinetic data from a shorter-term study in rats, the highest dose of 0.125 mg/kg/day was anticipated to give systemic exposure in rats approximately 2 times the AUC in acne patients treated with 2 mg/cm^2 of Tazarotene Foam 0.1% over a 15% body surface area.

A long-term topical application study of up to 0.1% tazarotene in a gel formulation in mice terminated at 88 weeks showed that dose levels of 0.05, 0.125, 0.25, and 1 mg/kg/day (reduced to 0.5 mg/kg/day for males after 41 weeks due to severe dermal irritation) revealed no apparent carcinogenic effects when compared with vehicle control animals. AUC at the highest dose in mice was 49 times the AUC in acne patients treated with 2 mg/cm^2 of Tazarotene Foam 0.1% over a 15% body surface area.

In evaluation of photocarcinogenicity, median time to onset of tumors was decreased and the number of tumors increased in hairless mice following chronic topical dosing with exposure to ultraviolet radiation at tazarotene concentrations of 0.001%, 0.005%, and 0.01% in a gel formulation for up to 40 weeks.

Mutagenesis:

Tazarotene was non-mutagenic in the Ames assay and did not produce structural chromosomal aberrations in a human lymphocyte assay. Tazarotene was non-mutagenic in the CHO/HGPRT mammalian cell forward gene mutation assay and was non-clastogenic in the in vivo mouse micronucleus test.

Impairment of Fertility:

No impairment of fertility was observed in rats when male animals were treated for 70 days prior to mating and female animals were treated for 14 days prior to mating and continuing through gestation and lactation with topical doses of tazarotene gel up to 0.125 mg/kg/day. Based on data from another study, the systemic drug exposure at the 0.125 mg/kg/day dose in rats would be equivalent to 7.6 times the AUC in acne patients treated with 2 mg/cm^2 of Tazarotene Foam 0.1% over a 15% body surface area.

No impairment of mating performance or fertility was observed in male rats treated for 70 days prior to mating with oral doses of up to 1 mg/kg/day tazarotene. AUC at the highest dose in rats was 23 times the AUC in acne patients treated with 2 mg/cm^2 of Tazarotene Foam 0.1% over a 15% body surface area.

No effect on parameters of mating performance or fertility was observed in female rats treated for 15 days prior to mating and continuing through gestation day 7 with oral doses of tazarotene up to 2 mg/kg/day. However, there was a significant decrease in the number of estrous stages and an increase in developmental effects at that dose [see Pregnancy (8.1)]. AUC at the highest dose in rats was 42 times the AUC in acne patients treated with 2 mg/cm^2 of Tazarotene Foam 0.1% over a 15% body surface area.

Reproductive capabilities of F1 animals, including F2 survival and development, were not affected by topical administration of tazarotene gel to female F0 parental rats from gestation day 16 through lactation day 20 at the maximum tolerated dose of 0.125 mg/kg/day. Based on data from another study, the AUC in rats would be equivalent to 7.6 times the AUC in acne patients treated with 2 mg/cm^2 of Tazarotene Foam 0.1% over a 15% body surface area.

14 CLINICAL STUDIES

In 2 multi-center, randomized, double-blind, vehicle-controlled trials, a total of 1,485 subjects with moderate-to-severe acne vulgaris were randomized 1:1 to Tazarotene Foam or vehicle applied once daily for 12 weeks. Acne severity was evaluated using lesion counts and the 6-point Investigator's Global Assessment (IGA) scale (see Table 2). At baseline, 80% of subjects were graded as "moderate" or Grade 3 and 20% were graded as "severe" or Grade 4 on the IGA scale. At baseline, subjects had an average of 79.8 total lesions of which the mean number of inflammatory lesions was 31.9 and the mean number of non-inflammatory lesions was 47.8. Subjects ranged in age from 12 to 45 years, with 860 (58%) subjects aged 12 to 17 years; 428 (29%) subjects aged 18 to 25 years; 143 (10%) subjects aged 26 to 35 years and 54 (4%) subjects aged 36 to 45 years. Subjects enrolled in the trials by race were white (77%), black (15%), Asian (4%), and other (4%). Hispanics comprised 18% of the population. An equal number of males (49%) and females (51%) were enrolled. Treatment success was defined as a score of "clear" (Grade 0) or "almost clear" (Grade 1) and at least 2-grade improvement from the baseline score to Week 12.

Table 2. Investigator's Global Assessment Scale
Grade | Description
0 | Clear | Clear skin with no inflammatory or non-inflammatory lesions.
1 | Almost clear | Rare non-inflammatory lesions with no more than rare papules.
2 | Mild | Greater than Grade 1, some non-inflammatory lesions with no more than a few inflammatory lesions (papules/pustules only, no nodular lesions).
3 | Moderate | Greater than Grade 2, up to many non-inflammatory lesions and may have some inflammatory lesions, but no more than one small nodular lesion.
4 | Severe | Greater than Grade 3, up to many non-inflammatory and inflammatory lesions, but no more than a few nodular lesions.
5 | Very severe | Many non-inflammatory and inflammatory lesions and more than a few nodular lesions. May have cystic lesions.

Absolute and percent reductions in lesion counts and the IGA scale after 12 weeks of treatment in these 2 trials are shown in Table 3. Each trial needed to have a statistically significant reduction in 2 out of 3 lesion counts at Week 12.

Table 3. Reductions in Lesion Counts and Improvements in Investigator's Global Assessment at Week 12
 | Trial 1 |  | Trial 2
 | Tazarotene Foam N = 371 | Vehicle Foam N = 372 | Tazarotene Foam N = 373 | Vehicle Foam N = 369
Inflammatory Lesions
Mean absolute reduction from Baseline | 18.0 | 14.0 | 18.0 | 15.0
Mean percent reduction from Baseline | 58% | 45% | 55% | 45%
Non-inflammatory Lesions
Mean absolute reduction from Baseline | 28.0 | 17.0 | 26.0 | 18.0
Mean percent reduction from Baseline | 55% | 33% | 57% | 41%
Total Lesions
Mean absolute reduction from Baseline | 46.0 | 31.0 | 43.0 | 33.0
Mean percent reduction from Baseline | 56% | 39% | 56% | 43%
Investigator's Global Assessment (IGA),
n (%) Minimum 2-Dgrade improvement and IGA of 0 or 1 | 107 (29%) | 60 (16%) | 103 (28%) | 49 (13%)

16 HOW SUPPLIED/STORAGE AND HANDLING

How Supplied:

Tazarotene Foam, 0.1% (1 mg/g) is a white to off-white foam, supplied as follows:

50-g aluminum can | NDC 68308-685-50

Storage and Handling:

- Store at 20°C to 25°C (68°F to 77°F); excursions permitted to 15°C to 30°C (59°F to 86°F). See USP-controlled room temperature.
- Store upright.
- Protect from freezing.
- Flammable. Avoid fire, flame, or smoking during and immediately following application. Contents under pressure. Do not puncture or incinerate. Do not expose to heat or store at temperatures above 120°F (49°C).
- Shake can before use. Hold can at an upright angle and press firmly to dispense.

17 PATIENT COUNSELING INFORMATION

See FDA-approved patient labeling (Patient Information).

Inform the patient of the following:

- Fetal risk associated with Tazarotene Foam for females of childbearing potential. Advise patients to use an effective method of contraception during treatment to avoid pregnancy. Advise the patient to stop medication if she becomes pregnant and call her doctor.
- If undue irritation (redness, peeling, or discomfort) occurs, reduce frequency of application or temporarily interrupt treatment. Treatment may be resumed once irritation subsides.
- Do not place Tazarotene Foam in the freezer.
- Avoid exposure of the treated areas to either natural or artificial sunlight, including tanning beds and sun lamps.
- Avoid contact with the eyes. If Tazarotene Foam gets in or near their eyes, to rinse thoroughly with water.
- Wash their hands after applying Tazarotene Foam.
- Avoid fire, flame, or smoking during and immediately following application since Tazarotene Foam is flammable.
- Keep out of the reach of children.
- Not for ophthalmic, oral, or intravaginal use.

Distributed by:
Mayne Pharma
Raleigh, NC 27609

141190

Pharmacist-Detach here and Give Instructions to Patient

Patient Information

Tazarotene Foam

IMPORTANT: For skin use only. Do not get Tazarotene Foam in your eyes, mouth, or vagina.

Read the Patient Information that comes with Tazarotene Foam before you start using it and each time you get a refill. There may be new information. This leaflet does not take the place of talking with your doctor about your medical condition or treatment.

What is Tazarotene Foam?

Tazarotene Foam is a prescription medicine used on the skin (topical) to treat acne in people 12 years and older.

It is not known if Tazarotene Foam is safe and effective in children under 12 years of age.

Who should not use Tazarotene Foam?

Do not use Tazarotene Foam if you are pregnant or plan to become pregnant. Tazarotene Foam may harm your unborn baby, if used during pregnancy.

If you are a female who can become pregnant:

- Use an effective method of birth control during treatment with Tazarotene Foam. Talk with your doctor about birth control methods that are right for you during treatment with Tazarotene Foam.
- Your doctor should do a blood or urine pregnancy test within 2 weeks before you begin to use Tazarotene Foam to be sure you are not pregnant.
- If you have menstrual periods, begin using Tazarotene Foam during a normal menstrual period to help assure that you are not pregnant when you begin use.

Stop using Tazarotene Foam and call your doctor right away if you become pregnant during treatment with Tazarotene Foam.

What should I tell my doctor before using Tazarotene Foam?

Before you use Tazarotene Foam, tell your doctor if you:

- or a family member have or had skin cancer.
- have eczema.
- have had a reaction to topical products in the past.
- have any condition that makes you sensitive to light.
- have any other medical conditions.
- are pregnant or plan to become pregnant. See "Who should not use Tazarotene Foam?"
- are breastfeeding or plan to breastfeed. It is not known if tazarotene passes into your breast milk. You and your doctor should decide if you will use Tazarotene Foam or breastfeed. You should not do both. Talk to your doctor about the best way to feed your baby if you use Tazarotene Foam.

Tell your doctor about all the medicines you take including prescription and nonprescription medicines, vitamins, and herbal supplements.

Especially tell your doctor if you:

- use other medicines or products that make your skin dry
- take other medicines that may increase your sensitivity to sunlight

Ask your doctor or pharmacist if you are not sure if your medicine is one that is listed above.

Know the medicines you take. Keep a list of your medicines and show it to your doctor and pharmacist when you get a new medicine.

How should I use Tazarotene Foam?

- Use Tazarotene Foam exactly as your doctor tells you to. Do not use more Tazarotene Foam than prescribed and do not use it more often than your doctor tells you to.
- If you are a female and have menstrual periods, begin using Tazarotene Foam during a normal menstrual period to help assure that you are not pregnant when you begin use. See "Who should not use Tazarotene Foam?"
- Tazarotene Foam is flammable. Avoid fire, flame, and smoking during and right after you apply Tazarotene Foam.
- Gently clean the affected area (face and/or upper trunk) with a mild cleanser and dry completely before using Tazarotene Foam.
- Apply Tazarotene Foam one time each day, before going to bed, to the affected areas (face and/or upper trunk) where you have acne lesions. Use enough foam to cover the entire affected area with a thin film of Tazarotene Foam.
- Keep Tazarotene Foam away from your eyes, mouth, and vagina. If Tazarotene Foam comes into contact with your eyes, rinse them well with water.
- Wash your hands after applying Tazarotene Foam.
- If you use too much Tazarotene Foam, you may get redness, peeling, or skin irritation in the treated area. Call your doctor if this happens, or if you accidentally swallow Tazarotene Foam.
- Follow your doctor's directions for other routine skin care and the use of make-up.
- You may also use a moisturizer as needed.

Instructions for applying Tazarotene Foam

1. Shake the Tazarotene Foam can before use.

2. Remove cap from can. See Figure A.

Figure A

3. Hold the Tazarotene Foam can upright at a slight angle and press the nozzle. See Figure B.

Figure B

4. Dispense a small amount of Tazarotene Foam into the palm of your hand. See Figure C.

Figure C

5. Use the fingertips of your other hand to apply enough Tazarotene Foam to cover the affected area with a thin layer. Gently rub the foam into the affected area until it disappears into the skin. See Figure D.

Figure D

6. Wash hands after applying Tazarotene Foam. See Figure E.

Figure E

Avoid getting Tazarotene Foam in your eyes, mouth, or vagina.

What should I avoid while using Tazarotene Foam?

- Avoid using abrasive soaps or cleansers that might dry or irritate your skin, unless your doctor tells you it is ok.
- Avoid sunlight. Tazarotene Foam can make your skin sensitive to sunlight and the light from sunlamps or tanning beds. You could get a sunburn. Use sunscreen and protective clothing during the day if you must be in sunlight.
- Avoid using Tazarotene Foam if you have a sunburn. If you have a sunburn, wait until it is fully healed before using Tazarotene Foam.
- Talk to your doctor before using Tazarotene Foam if you are sensitive to sunlight, take medications that increase your sensitivity to sunlight, or you must spend a lot of time in the sun for your job.
- Avoid weather extremes, such as wind and cold, because they may irritate your skin more while you are using Tazarotene Foam.

What are the possible side effects of Tazarotene Foam?

Tazarotene Foam may harm your unborn baby, if used during pregnancy.

- Do not use Tazarotene Foam during pregnancy. See "Who should not use Tazarotene Foam?"

The most common side effects of Tazarotene Foam are:

- burning or stinging
- dry skin
- red skin
- peeling or flaking skin

Sometimes these symptoms can become severe and may be uncomfortable. Tell your doctor if these side effects become uncomfortable for you. Your doctor may tell you to stop using Tazarotene Foam until your skin heals and your symptoms improve, or to use Tazarotene Foam less often to help you tolerate it better.

These are not all the possible side effects of Tazarotene Foam. For more information, ask your doctor or pharmacist.

Call your doctor for medical advice about side effects. You may report side effects to FDA at 1-800- FDA-1088.

You may also report side effects to Mayne Pharma at 1-844-825-8500.

How should I store Tazarotene Foam?

- Store Tazarotene Foam at room temperature, between 68°F to 77°F (20°C to 25°C).
- Store Tazarotene Foam upright.
- Do not freeze Tazarotene Foam.
- Tazarotene Foam is flammable. Keep the can away from fire and heat. Do not spray Tazarotene Foam near fire or direct heat.
- Do not puncture the can or throw it into a fire, even if the can is empty.

Keep Tazarotene Foam and all medicines out of the reach of children. General Information about Tazarotene Foam

Medicines are sometimes prescribed for purposes other than those listed in Patient Information leaflets. Do not use Tazarotene Foam for a condition for which it was not prescribed. Do not give Tazarotene Foam to other people even if they have the same symptoms that you have. It may harm them.

This Patient Information leaflet summarizes the most important information about Tazarotene Foam. If you would like more information, talk with your doctor. You can ask your doctor or pharmacist for information about Tazarotene Foam that is written for health professionals.

What are the ingredients in Tazarotene Foam?

Active ingredient: tazarotene

Inactive ingredients: butylated hydroxytoluene, ceteareth-12, citric acid anhydrous, diisopropyl adipate, light mineral oil, potassium citrate monohydrate, potassium sorbate, purified water, and sorbic acid. The foam is dispensed from an aluminum can pressurized with a hydrocarbon (propane/n-butane/isobutane) propellant.

This Patient Information has been approved by the U.S. Food and Drug Administration.

Distributed by:
Mayne Pharma
Raleigh, NC 27609

03/2023

PRINCIPAL DISPLAY PANEL - 50 grams Can Carton

NDC 68308-685-50

Tazarotene

Foam, 0.1%

50 grams

Rx only
For topical use only

STORE UPRIGHT

mayne pharma

Recyclable
Aluminum
Container